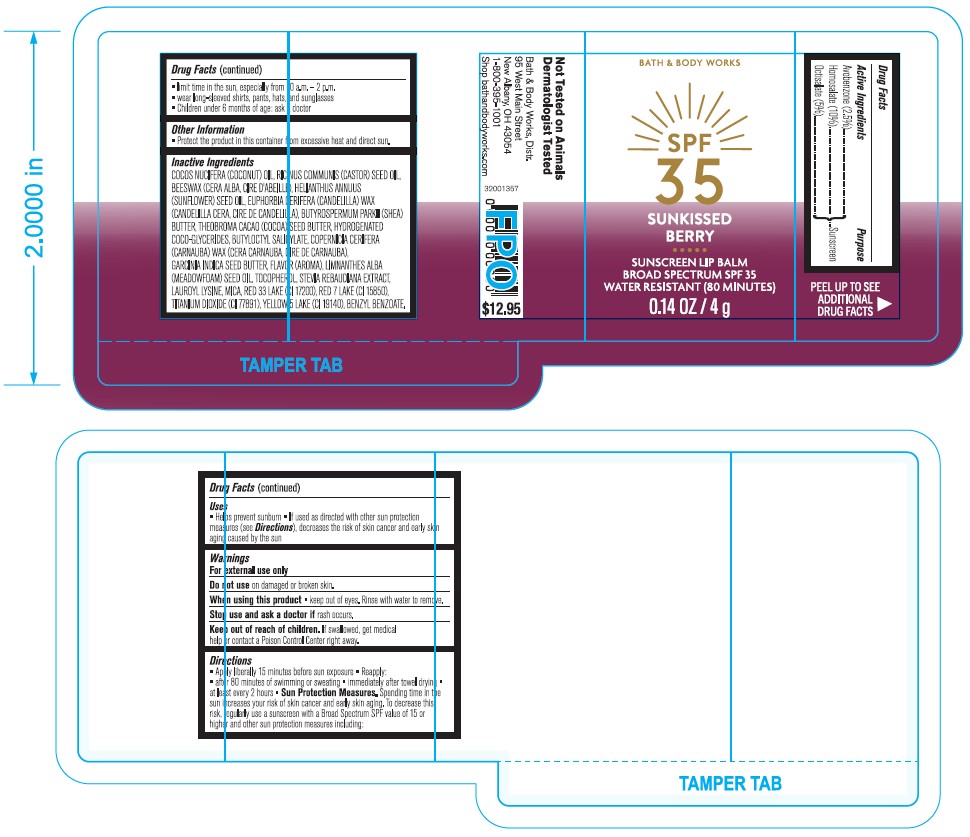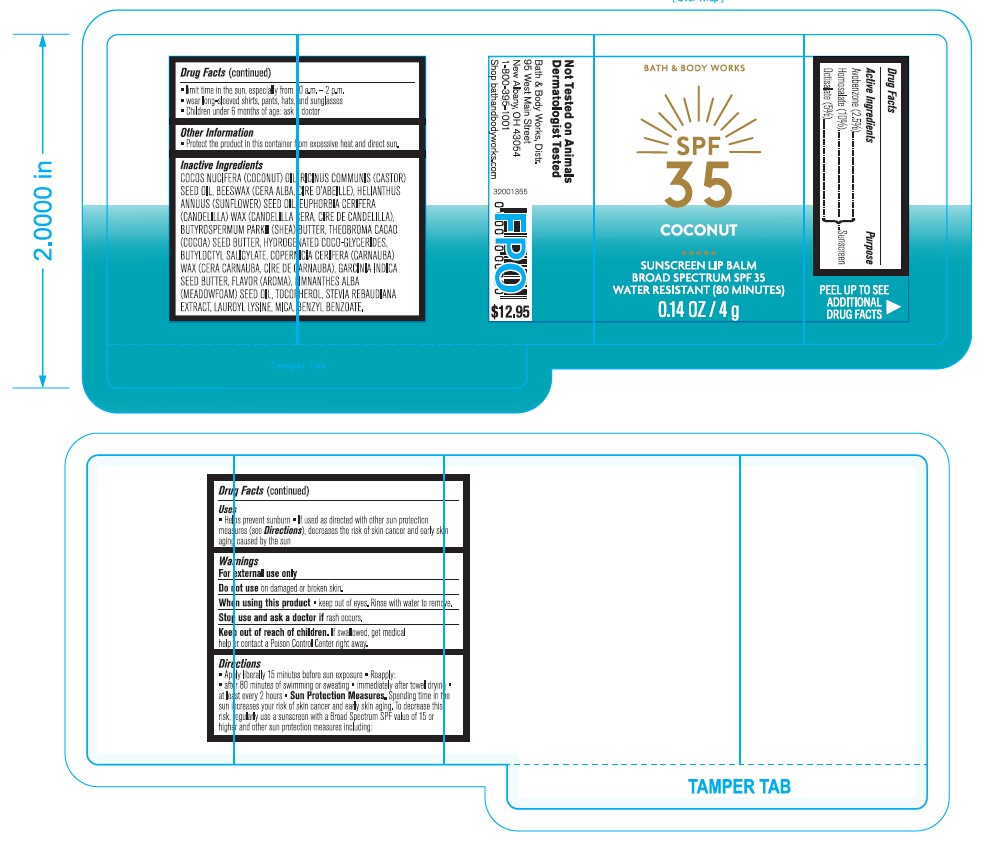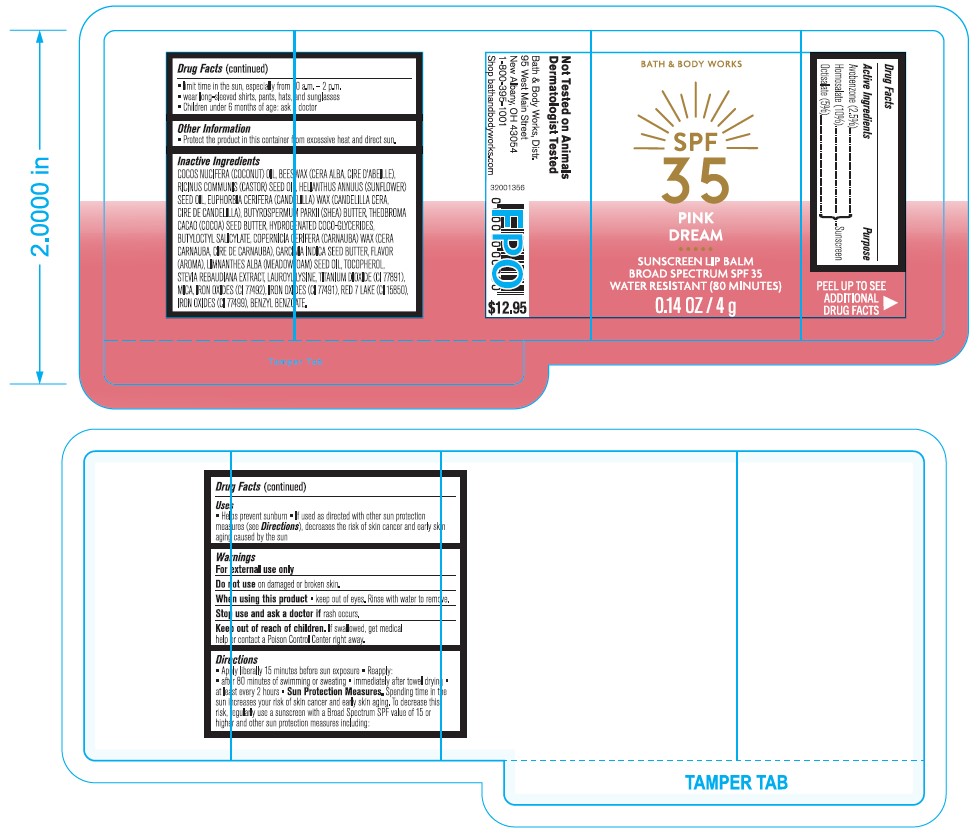 DRUG LABEL: BBW SPF 35 Pink Dream Lip Balm
NDC: 51514-0367 | Form: STICK
Manufacturer: Autumn Harp
Category: otc | Type: HUMAN OTC DRUG LABEL
Date: 20240122

ACTIVE INGREDIENTS: HOMOSALATE 10 g/100 g; OCTISALATE 5 g/100 g; AVOBENZONE 2.5 g/100 g
INACTIVE INGREDIENTS: YELLOW WAX; SUNFLOWER OIL; HYDROGENATED COCO-GLYCERIDES; LAUROYL LYSINE; BENZYL ALCOHOL; CASTOR OIL; BUTYLOCTYL SALICYLATE; MICA; SOYBEAN OIL; CANDELILLA WAX; SHEA BUTTER; COCOA BUTTER; GARCINIA INDICA SEED BUTTER; MEADOWFOAM SEED OIL; .ALPHA.-TOCOPHEROL, DL-; BENZYL SALICYLATE; CARNAUBA WAX; BENZYL BENZOATE; STEVIA REBAUDIUNA LEAF; ANISE OIL; COCONUT OIL; TITANIUM DIOXIDE; FERRIC OXIDE RED; FERROSOFERRIC OXIDE; FERRIC OXIDE YELLOW

Bath and Body Works SPF 35 Lip Balm

ACTIVE INGREDIENT

Avobenzone 2.5%

Homosalate 10%

Octisalate 5%

PURPOSE

Avobenzone - Sunscreen

Homosalate - Sunscreen

Octisalate - Sunscreen

DOSAGE AND ADMINISTRATION

Apply liberally 15 minutes before sun exposure. Reapply:

- After 80 minutes of swimming or sweating
- Immediately after towel drying
- at least every 2 hours

WARNINGS

For external use only

Do not use on domaged or broken skin

When using this product, keep out of eyes. Rinse with water to remove

Sop use and ask a doctor if rash occurs

INSTRUCTIONS FOR USE

Protect the product in this container from excessive heat and direct sun

OTHER SAFETY INFORMATION

Limit time in the sun, especially from 10am - 2pm

Wear long sleeved shirts, pants, hats and sunglasses

Children under 6 months of age: ask a doctor

INACTIVE INGREDIENT

Natural Inactive Ingredients: Cocos Nucifera (Coconut) Oil, Ricinus Communis (Castor) Seed Oil, Beeswax, Helianthus Annuus (Sunflower) Seed Oil, Euphorbia Cerifera (Candelilla) Wax, Butyrospermum Parkii (Shea) Butter, Theobroma Cacao (Cocoa) Seed Butter, Butyloctyl Salicylate, Hydrogenated Coco-Glycerides, Copernicia Cerifera (Carnauba) Wax, Garcinia Indica Seed Butter, Flavor, Limnanthes Alba (Meadowfoam) Seed Oil, Benzyl Benzoate, Mica, Tocopherol, Stevia Rebaudiana Leaf/Stem Extract, Lauroyl Lysine, Glycine Soja (Soybean) Oil, Benzyl Alcohol, Benzyl Salicylate.

Berry Inactive Ingredients: Cocos Nucifera (Coconut) Oil, Ricinus Communis (Castor) Seed Oil, Beeswax, Helianthus Annuus (Sunflower) Seed Oil, Euphorbia Cerifera (Candelilla) Wax, Butyrospermum Parkii (Shea) Butter, Theobroma Cacao (Cocoa) Seed Butter, Butyloctyl Salicylate, Hydrogenated Coco-Glycerides, Copernicia Cerifera (Carnauba) Wax, Garcinia Indica Seed Butter, Flavor, Limnanthes Alba (Meadowfoam) Seed Oil, Benzyl Benzoate, Mica, Red 33 Lake (CI 17200), Red 7 Lake (CI 15850), Titanium Dioxide (CI 77891), Yellow 5 Lake (CI 19140), Tocopherol, Stevia Rebaudiana Leaf/Stem Extract, Lauroyl Lysine, Glycine Soja (Soybean) Oil, Benzyl Alcohol, Benzyl Salicylate.

Summer Crush Inactive Ingredients: Cocos Nucifera (Coconut) Oil, Beeswax, Ricinus Communis (Castor) Seed Oil, Helianthus Annuus (Sunflower) Seed Oil, Euphorbia Cerifera (Candelilla) Wax, Butyrospermum Parkii (Shea) Butter, Theobroma Cacao (Cocoa) Seed Butter, Butyloctyl Salicylate, Hydrogenated Coco-Glycerides, Copernicia Cerifera (Carnauba) Wax, Garcinia Indica Seed Butter, Titanium Dioxide (CI 77891), Flavor, Limnanthes Alba (Meadowfoam) Seed Oil, Benzyl Benzoate, Mica, Iron Oxide (CI 77492), Iron Oxides (CI 77491), Red 7 Lake (CI 15850), Tocopherol, Iron Oxides (CI77499), Stevia Rebaudiana Leaf/Stem Extract, Lauroyl Lysine, Glycine Soja (Soybean) Oil, Benzyl Alcohol, Benzyl Salicylate.

QUESTIONS

1-800-395-1001

INDICATIONS AND USAGE

Helps prevent sunburn if used as directed with other sun protection measures (see Directions), decreases the risk of skin cancer and early skin aging caused by the sun

Keep out of reach of children. If swallowed, get medical help or contact a Poison Control Center right away.